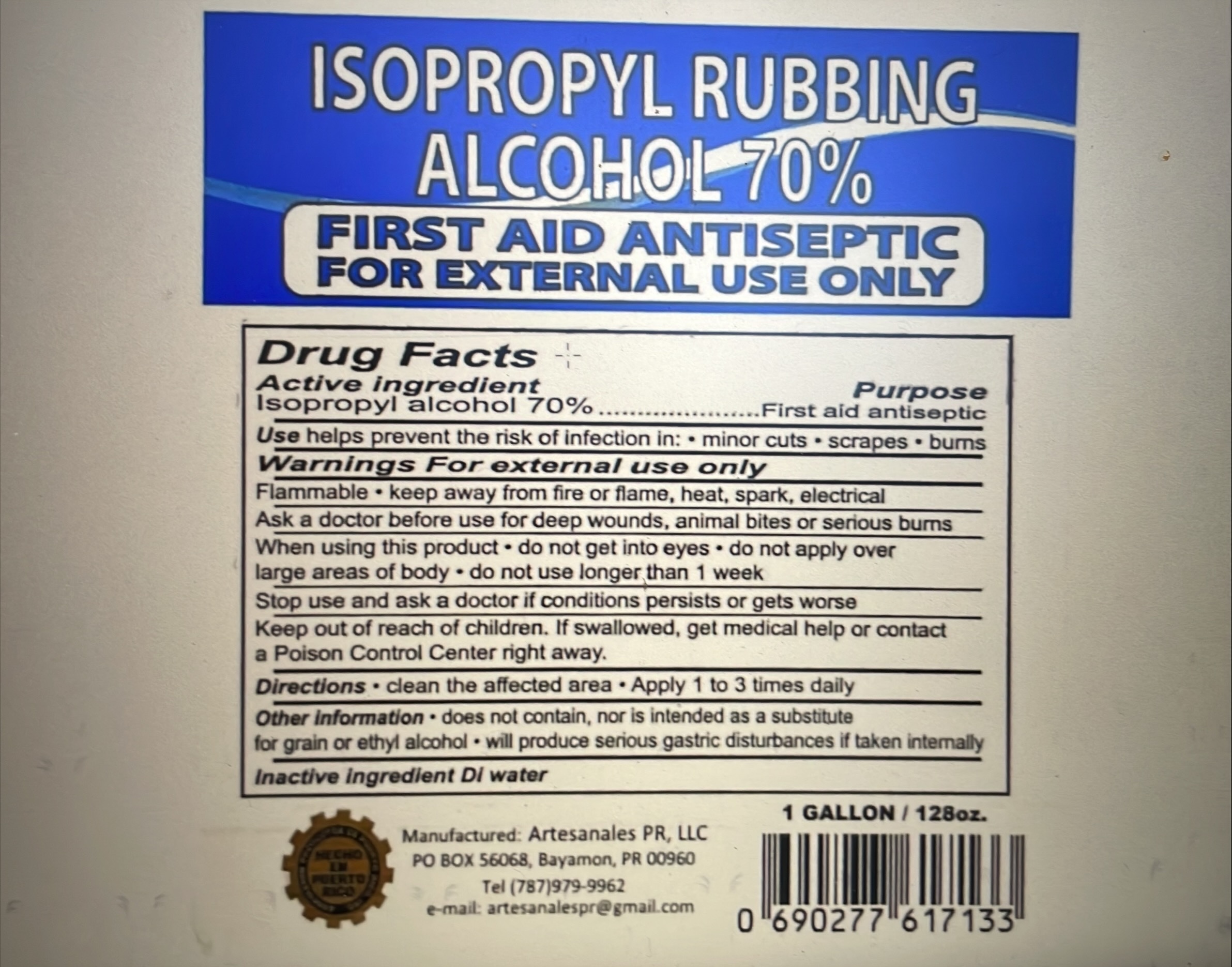 DRUG LABEL: ISOPROPYL RUBBING ALCOHOL 70%
NDC: 78824-625 | Form: LIQUID
Manufacturer: Artesanales P.R. LLC
Category: otc | Type: HUMAN OTC DRUG LABEL
Date: 20240103

ACTIVE INGREDIENTS: ISOPROPYL ALCOHOL 70 mL/99 mL
INACTIVE INGREDIENTS: WATER

The hand sanitizer is manufactured using grade ingredients:

Isopropyl Alcohol (USP or Food Chemical Codex) (99% (v/v) in an aqueous solution

water

the firm does not add other active or inactive ingredients. Different or additional ingredients may impact the quality and potency of the product.

ACTIVE INGREDIENT

Isopropyl Alcohol 99% v/v. Purpose: Antiseptic

PURPOSE

Antiseptic, Hand Sanitizer

INDICATIONS AND USAGE

Hand Sanitizer to help reduce bacteria that can potentially cause a disease. For use when soap and water are not available

DO NOT USE

in children less than 2 onths of age

on open skin wounds

WARNINGS

For external use only. Flammable. Keep away from heat or flame

When using this product keep out of eyes, ears, and mouth. In case of contact with eyes, rinse eyes thoroughly with water.

Stop use and ask a doctor if irritation or rash occurs. These may be signs of a serious condition.

Keep out of reach of children. If swallowed, get medical help or contact a Poison Control Center right away.

Stop use and ask a doctor if irrittion or rash occurs. These may be signs of a serious condition

Keep out of reach of children. If swallowed, get medical help or contact a Poison Control Center right away.

DOSAGE AND ADMINISTRATION

Place enough product on hands to cover all surfaces. Rub hands together until dry. Supervise children under 6 years of age when using this product to avoid swallowing.

STORAGE AND HANDLING

store between 15-30C (59-86F)

avoid freezing and excessive heat above 40C (104F)

INACTIVE INGREDIENT

water